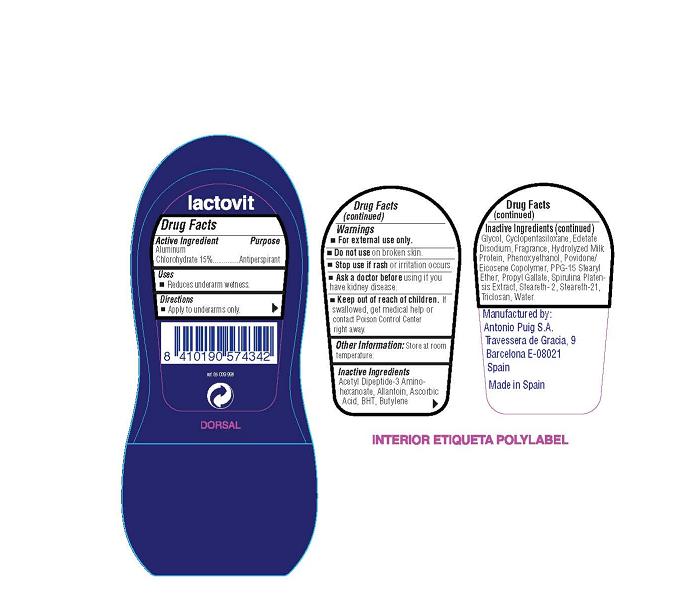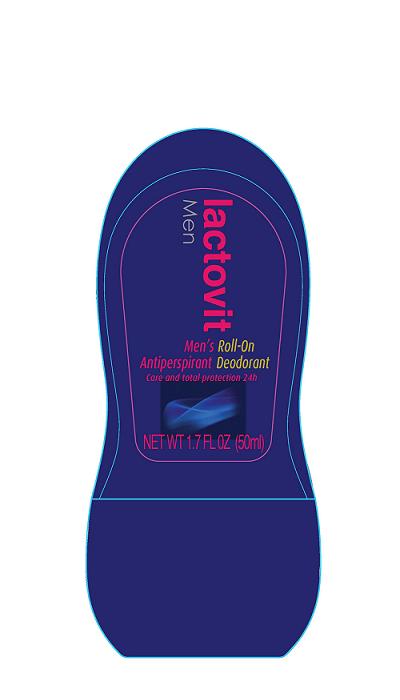 DRUG LABEL: Lactovit Men Roll-On Antiperspirant Deodorant
NDC: 50007-3000 | Form: LIQUID
Manufacturer: Antonio Puig, S.A.
Category: otc | Type: HUMAN OTC DRUG LABEL
Date: 20091216

ACTIVE INGREDIENTS: ALUMINUM CHLOROHYDRATE 15 mL/100 mL
INACTIVE INGREDIENTS: ALLANTOIN; ASCORBIC ACID; BUTYLATED HYDROXYTOLUENE; BUTYLENE GLYCOL; CYCLOMETHICONE 5; EDETATE DISODIUM; PHENOXYETHANOL; PROPYL GALLATE; TRICLOSAN; WATER

Lactovit Men - Aluminum Chlorohydrate

Active Ingredient

Aluminum Chlorohydrate 15 percent

Purpose

Antiperspirant

Uses

- Reduces underarm wetness.

Directions

- Apply to underarms only.

WARNINGS

- For external use only.

- Do not use on broken skin.

- Stop use if rash or irritation occurs.

- Ask a doctor before using if you have kidney disease.

- Keep out of reach of children. If swallowed, get medical help or
contact Poison Control Center right away.

Other Information:

Store at room temperature.

Inactive Ingredients

Acetyl Dipeptide-3 Amino-hexanoate, Allantoin, Ascorbic Acid, BHT,

Butylene Glycol, Cyclopentasiloxane, Edetate Disodium, Fragrance,

Hydrolyzed Milk Protein, Phenoxyethanol, Povidone/Eicosene Copolymer,

PPG-15 Stearyl Ether, Propyl Gallate, Spirulina Platensis Extract, Steareth-2,

Steareth-21, Triclosan, Water

PACKAGE LABEL

Manufactured by:

Antonio Puig S.A.

Travessera de Gracia, 9

Barcelona E-08021

Spain

Made in Spain